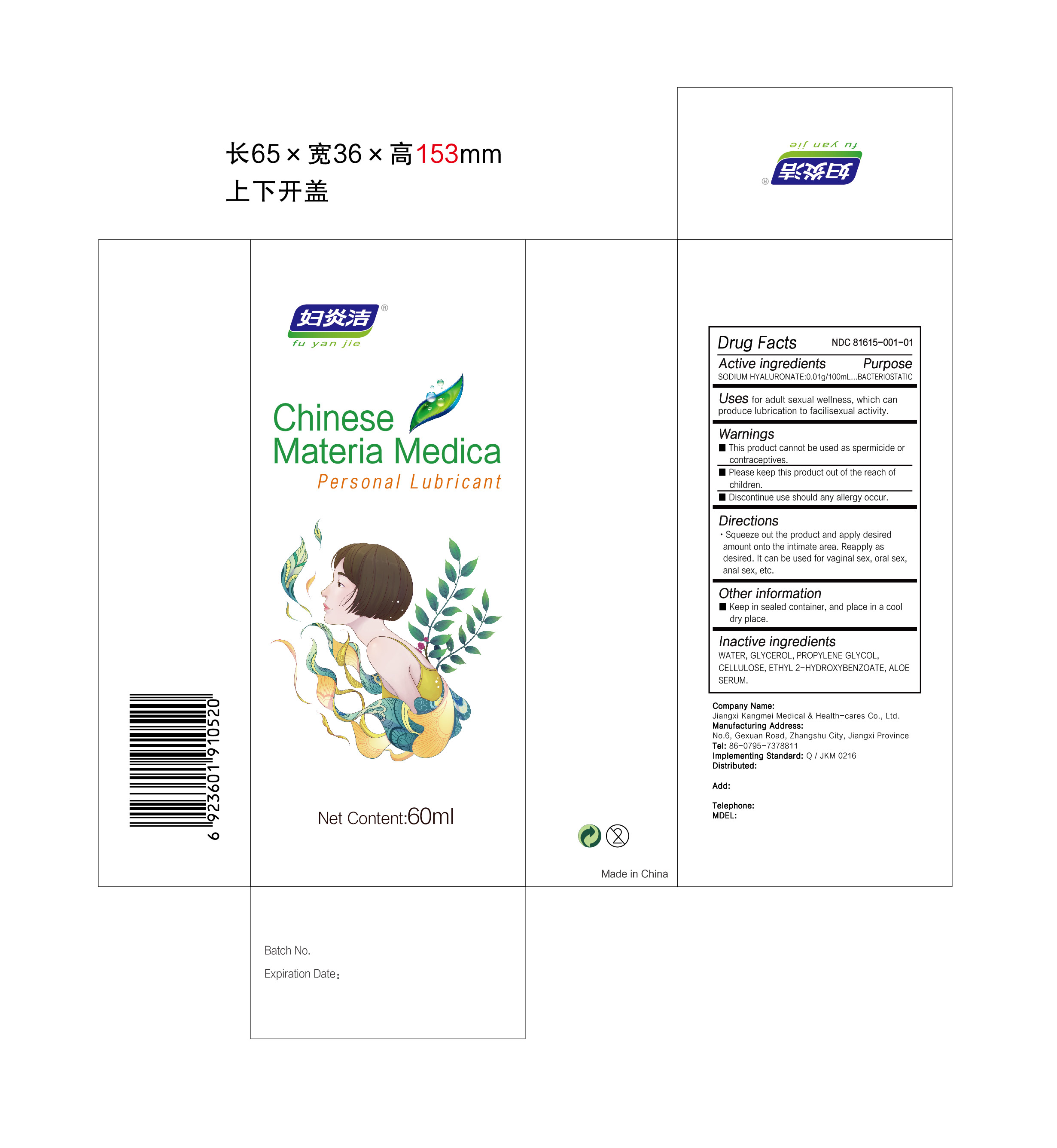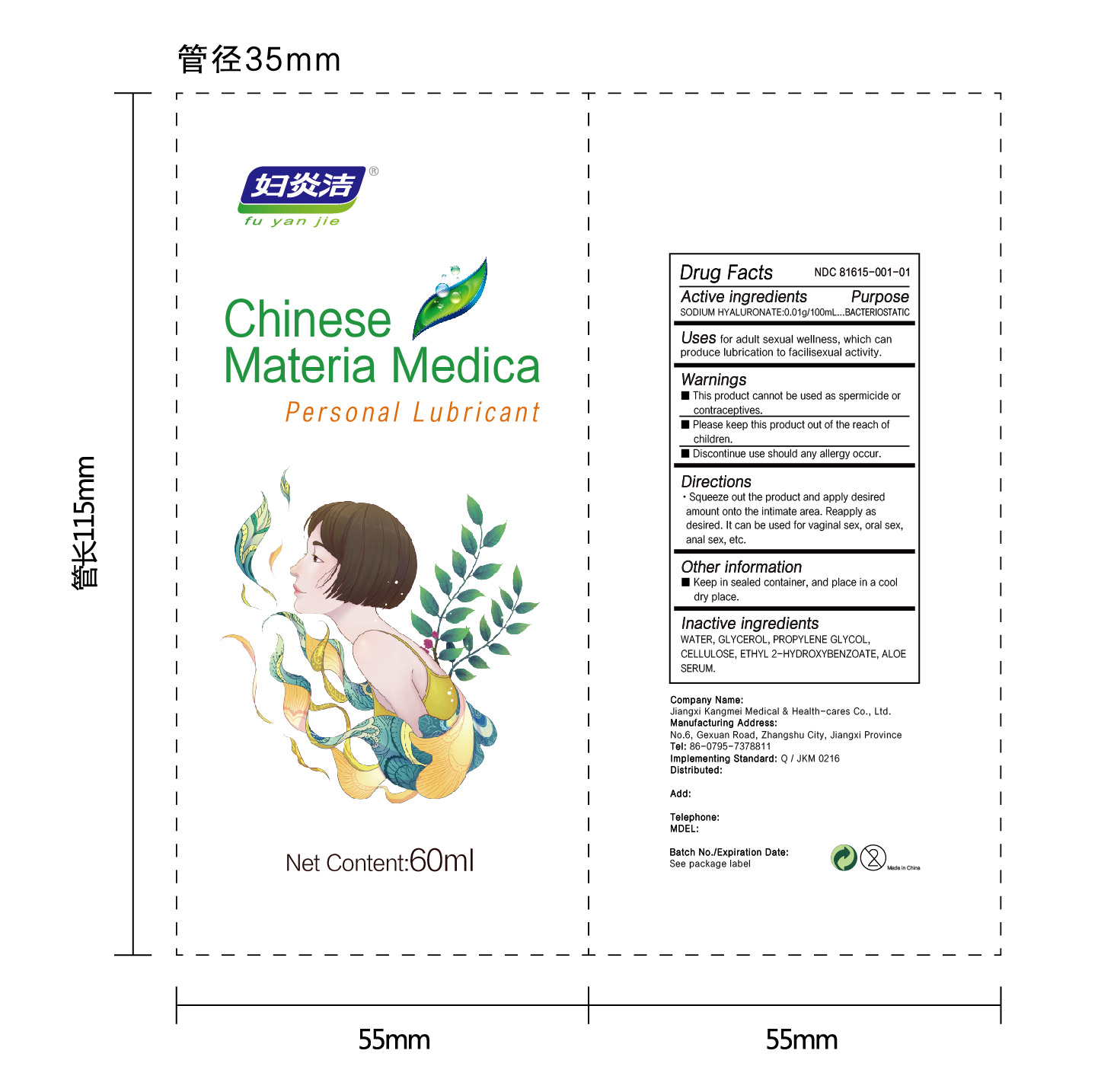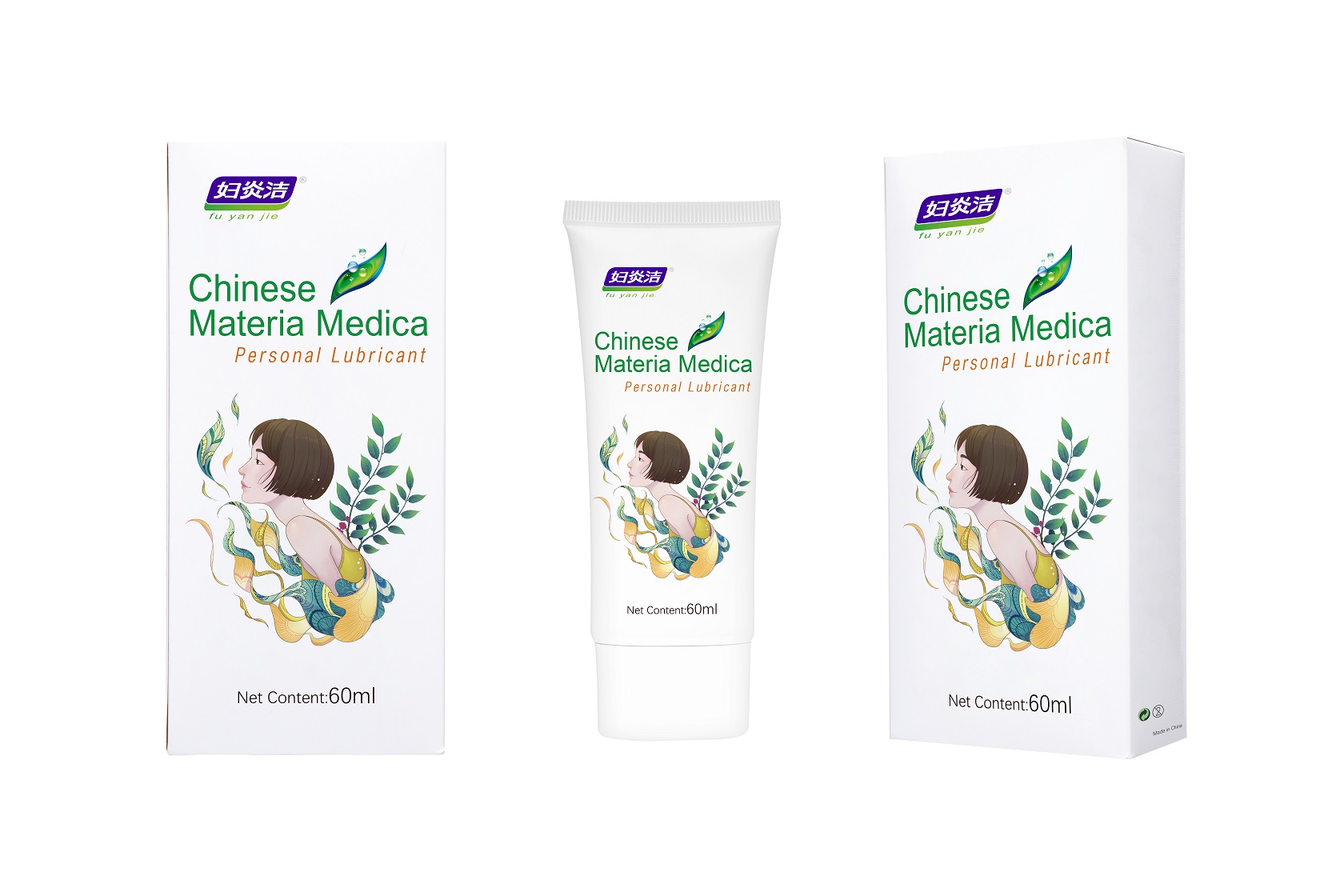 DRUG LABEL: PERSONAL LUBRICANT
NDC: 81615-001 | Form: GEL
Manufacturer: Jiangxi Renhetang pharmaceutical chain Co., Ltd.
Category: otc | Type: HUMAN OTC DRUG LABEL
Date: 20210420

ACTIVE INGREDIENTS: HYALURONATE SODIUM 0.01 g/100 mL
INACTIVE INGREDIENTS: ALOE VERA LEAF; POWDERED CELLULOSE; GLYCERIN; PROPYLENE GLYCOL; WATER; ETHYL SALICYLATE

PERSONAL LUBRICANT

PERSONAL LUBRICANT

Active Ingredient(s)

SODIUM HYALURONATE 0.01g/100mL

Purpose

BACTERIOSTATIC

Use

Uses for adult sexual wellness, which can produce lubrication to facilisexual activity.

Warnings

This product cannot be used as spermicide or contraceptives.

Please keep this product out of the reach of children.

Discontinue use should any allergy occur.

When using this product keep out of eyes, ears, and mouth. In case of contact with eyes, rinse eyes thoroughly with water.
Stop use and ask a doctor if irritation or rash occurs. These may be signs of a serious condition.
Keep out of reach of children. If swallowed, get medical help or contact a Poison Control Center right away.

Stop use and ask a doctor if irritation or rash occurs. These may be signs of a serious condition.

Keep out of reach of children. If swallowed, get medical help or contact a Poison Control Center right away.

Directions

- Squeeze out the product and apply desired amount onto the intimate area. Reapply as desired. It can be used for vaginal sex, oral sex, anal sex, etc.

Other information

- Keep in sealed container, and place in a cool dry place.

Inactive ingredients

WATER, GLYCEROL, PROPYLENE GLYCOL, CELLULOSE, SODIUM HYALURONATE, ETHYL 2-HYDROXYBENZOATE, ALOE SERUM.